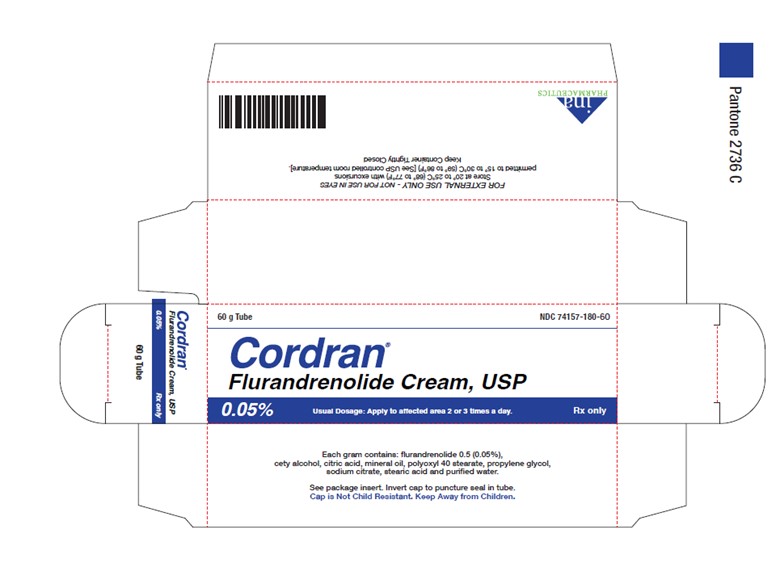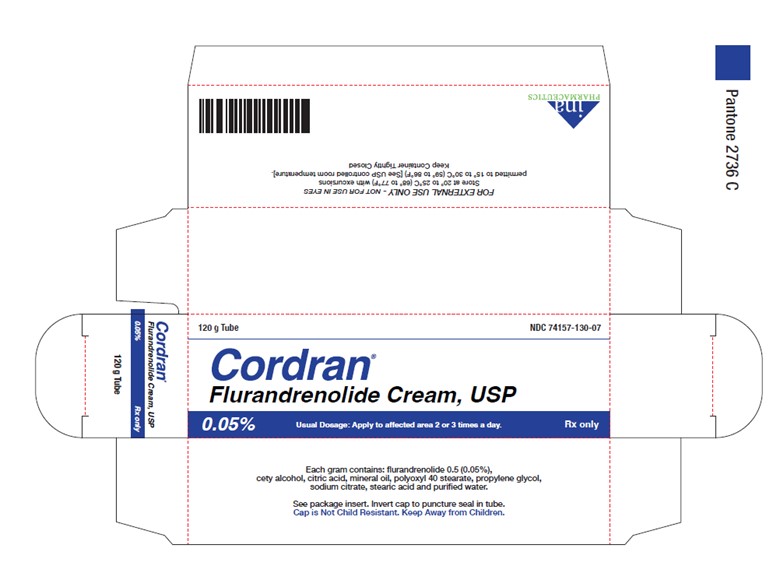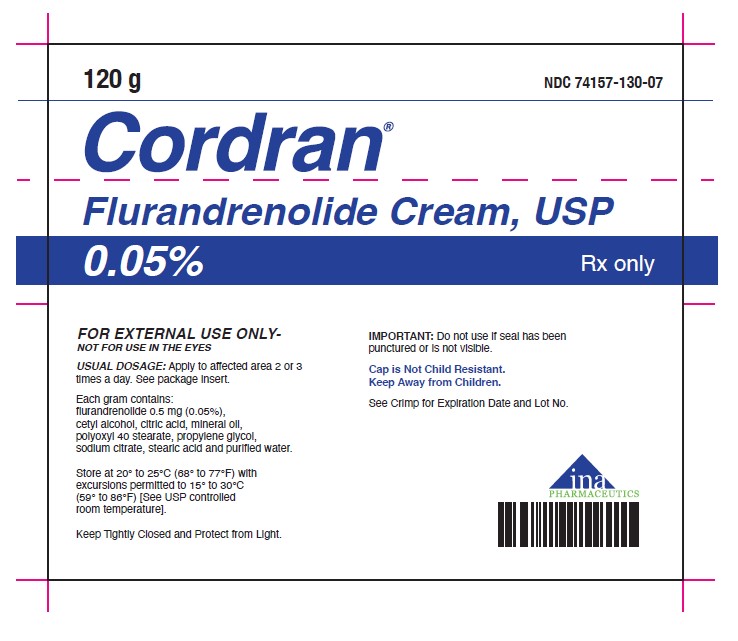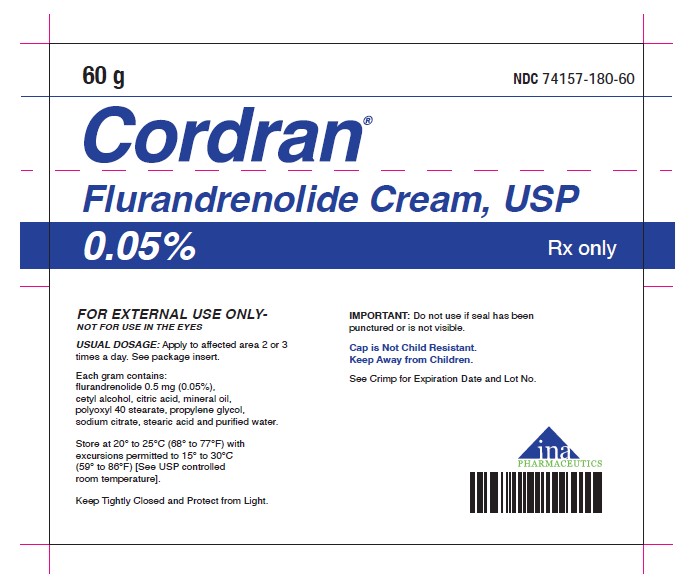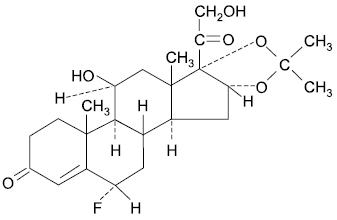 DRUG LABEL: CORDRAN
NDC: 74157-130 | Form: CREAM
Manufacturer: INA Pharmaceutics, Inc
Category: prescription | Type: HUMAN PRESCRIPTION DRUG LABEL
Date: 20250707

ACTIVE INGREDIENTS: FLURANDRENOLIDE 0.5 mg/1 g
INACTIVE INGREDIENTS: CETYL ALCOHOL; CITRIC ACID MONOHYDRATE; MINERAL OIL; POLYOXYL 40 STEARATE; PROPYLENE GLYCOL; SODIUM CITRATE, UNSPECIFIED FORM; STEARIC ACID; WATER

Cordran® Cream
Flurandrenolide, USP

DESCRIPTION

Cordran® (flurandrenolide, USP) is a potent corticosteroid intended for topical use. Flurandrenolide occurs as white to off-white, fluffy, crystalline powder and is odorless. Flurandrenolide is practically insoluble in water and in ether. One gram of flurandrenolide dissolves in 72 mL of alcohol and in 10 mL of chloroform. The molecular weight of flurandrenolide is 436.52.

The chemical name of flurandrenolide is Pregn-4-ene-3,20-dione, 6-fluoro-11,21-dihydroxy- 16,17-[(1-methylethylidene)bis (oxy)]-, (6α, 11β, 16α)-; its empirical formula is C24H33FO6. The structure is as follows:

Each gram of Cordran® Cream (flurandrenolide Cream, USP) contains 0.5 mg (1.145 μmol; 0.05%) flurandrenolide in an emulsified base composed of cetyl alcohol, citric acid, mineral oil, polyoxyl 40 stearate, propylene glycol, sodium citrate, stearic acid, and purified water.

CLINICAL PHARMACOLOGY

Cordran is primarily effective because of its anti-inflammatory, antipruritic, and vasoconstrictive actions.

The mechanism of the anti-inflammatory effect of topical corticosteroids is not completely understood. Corticosteroids with anti-inflammatory activity may stabilize cellular and lysosomal membranes. There is also the suggestion that the effect on the membranes of lysosomes prevents the release of proteolytic enzymes and, thus, plays a part in reducing inflammation.

Pharmacokinetics

The extent of percutaneous absorption of topical corticosteroids is determined by many factors, including the vehicle, the integrity of the epidermal barrier, and the use of occlusive dressings.

Topical corticosteroids can be absorbed from normal intact skin. Inflammation and/or other disease processes in the skin increase percutaneous absorption.

Once absorbed through the skin, topical corticosteroids are handled through pharmacokinetic pathways similar to systemically administered corticosteroids. Corticosteroids are bound to plasma proteins in varying degrees. They are metabolized primarily in the liver and then excreted in the kidneys. Some of the topical corticosteroids and their metabolites are also excreted into the bile.

INDICATIONS AND USAGE

Cordran® (flurandrenolide, USP) is indicated for the relief of the inflammatory and pruritic manifestations of corticosteroid-responsive dermatoses.

CONTRAINDICATIONS

Topical corticosteroids are contraindicated in patients with a history of hypersensitivity to any of the components of these preparations.

PRECAUTIONS

General

Systemic absorption of topical corticosteroids has produced reversible hypothalamic-pituitary-adrenal (HPA) axis suppression, manifestations of Cushing's syndrome, hyperglycemia, and glucosuria in some patients.

Conditions that augment systemic absorption include application of the more potent steroids, use over large surface areas, prolonged use, and the addition of occlusive dressings.

Therefore, patients receiving a large dose of a potent topical steroid applied to a large surface area or under an occlusive dressing should be evaluated periodically for evidence of HPA axis suppression using urinary-free cortisol and ACTH stimulation tests. If HPA axis suppression is noted, an attempt should be made to withdraw the drug, to reduce the frequency of application, or to substitute a less potent steroid.

Recovery of HPA axis function is generally prompt and complete upon discontinuation of the drug. Infrequently, signs and symptoms of steroid withdrawal may occur, so that supplemental systemic corticosteroids are required.

Pediatric patients may absorb proportionately larger amounts of topical corticosteroids and thus be more susceptible to systemic toxicity (see Pediatric Use under PRECAUTIONS).

If irritation develops, topical corticosteroids should be discontinued and appropriate therapy instituted.

In the presence of dermatologic infections, the use of an appropriate antifungal or antibacterial agent should be instituted. If a favorable response does not occur promptly, Flurandrenolide cream should be discontinued until the infection has been adequately controlled.

Information for the Patient

Patients using topical corticosteroids should receive the following information and instructions:

1. This medication is to be used as directed by the physician. It is for external use only. Avoid contact with the eyes.
2. Patients should be advised not to use this medication for any disorder other than that for which it was prescribed.
3. The treated skin area should not be bandaged or otherwise covered or wrapped in order to be occlusive unless the patient is directed to do so by the physician.
4. Patients should report any signs of local adverse reactions, especially under occlusive dressing.
5. Parents of pediatric patients should be advised not to use tight-fitting diapers or plastic pants on a patient being treated in the diaper area, because these garments may constitute occlusive dressings.
6. Do not use Flurandrenolide cream on the face, underarms, or groin areas unless directed by your physician.
7. If no improvement is seen within 2 weeks, contact your physician.
8. Do not use other corticosteroid-containing products while using Cordran without first consulting your physician.

Laboratory Tests

The following tests may be helpful in evaluating the HPA axis suppression:

Urinary-free cortisol test
ACTH stimulation test

Carcinogenesis, Mutagenesis, and Impairment of Fertility

Long-term animal studies have not been performed to evaluate the carcinogenic potential or the effect on fertility of topical corticosteroids.

Studies to determine mutagenicity with prednisolone and hydrocortisone have revealed negative results.

Usage in Pregnancy

Pregnancy Category C

Corticosteroids are generally teratogenic in laboratory animals when administered systemically at relatively low dosage levels. The more potent corticosteroids have been shown to be teratogenic after dermal application in laboratory animals. There are no adequate and well-controlled studies in pregnant women on teratogenic effects from topically applied corticosteroids. Therefore, topical corticosteroids should be used during pregnancy only if the potential benefit justifies the potential risk to the fetus. Drugs of this class should not be used extensively for pregnant patients or in large amounts or for prolonged periods of time.

Nursing Mothers

It is not known whether topical administration of corticosteroids could result in sufficient systemic absorption to produce detectable quantities in breast milk. Systemically administered corticosteroids are secreted into breast milk in quantities notlikely to have a deleterious effect on the infant. Nevertheless, caution should be exercised when topical corticosteroids are administered to a nursing woman.

Pediatric Use

Pediatric patients may demonstrate greater susceptibility to topical corticosteroid-induced HPA axis suppression and Cushing's syndrome than do mature patients because of a larger skin surface area to body weight ratio.

Hypothalamic-pituitary-adrenal (HPA) axis suppression, Cushing's syndrome, and intracranial hypertension have been reported in pediatric patients receiving topical corticosteroids. Manifestations of adrenal suppression in pediatric patients include linear growth retardation, delayed weight gain, low plasma cortisol levels, and absence of response to ACTH stimulation. Manifestations of intracranial hypertension include bulging fontanelles, headaches, and bilateral papilledema.

Administration of topical corticosteroids to pediatric patients should be limited to the least amount compatible with an effective therapeutic regimen. Chronic corticosteroid therapy may interfere with the growth and development of pediatric patients.

ADVERSE REACTIONS

The following local adverse reactions are reported infrequently with topical corticosteroids but may occur more frequently with the use of occlusive dressings. These reactions are listed in an approximate decreasing order of occurrence:

Burning
Itching
Irritation
Dryness
Folliculitis
Hypertrichosis
Acneform eruptions
Hypopigmentation
Perioral dermatitis
Allergic contact dermatitis

The following may occur more frequently with occlusive dressings:

Maceration of the skin
Secondary infection
Skin atrophy
Striae
Miliaria

Postmarketing Adverse Reactions

The following adverse reactions have been identified during post approval use of flurandrenolide, USP. Because these reactions are reported voluntarily from a population of uncertain size, it is not always possible to reliably estimate their frequency or establish a causal relationship to drug exposure.

Skin: skin striae, hypersensitivity, skin atrophy, contact dermatitis and skin discoloration.

OVERDOSAGE

Topically applied corticosteroids can be absorbed in sufficient amounts to produce systemic effects (see PRECAUTIONS).

DOSAGE AND ADMINISTRATION

For moist lesions, a small quantity of the cream should be rubbed gently into the affected areas 2 or 3 times a day.

Therapy should be discontinued when control is achieved. If no improvement is seen within 2 weeks, reassessment of the diagnosis may be necessary.

Cordran® (flurandrenolide, USP) should not be used with occlusive dressings unless directed by a physician. Tight-fitting diapers or plastic pants may constitute occlusive dressings.

HOW SUPPLIED

Cordran® Cream is supplied in aluminum tubes as follows:

Flurandrenolide Cream, USP 0.05%:

60 g (NDC 74157-180-60)

120 g (NDC 74157-130-07)

Keep out of reach of children.

Storage

Keep tightly closed.

Protect from light.

Store at 20° to 25°C (68° to 77°F) with excursions permitted to 15° to 30°C (59° to 86°F) [See USP controlled room temperature].

Rx Only

Revision: July 2025

INA Pharmaceutics, Inc.

Manufactured by DPT Laboratories, San Antonio, TX 78215

PRINCIPAL DISPLAY PANEL

NDC 74157-180-60
60 g

NDC 74157-130-07
120 g